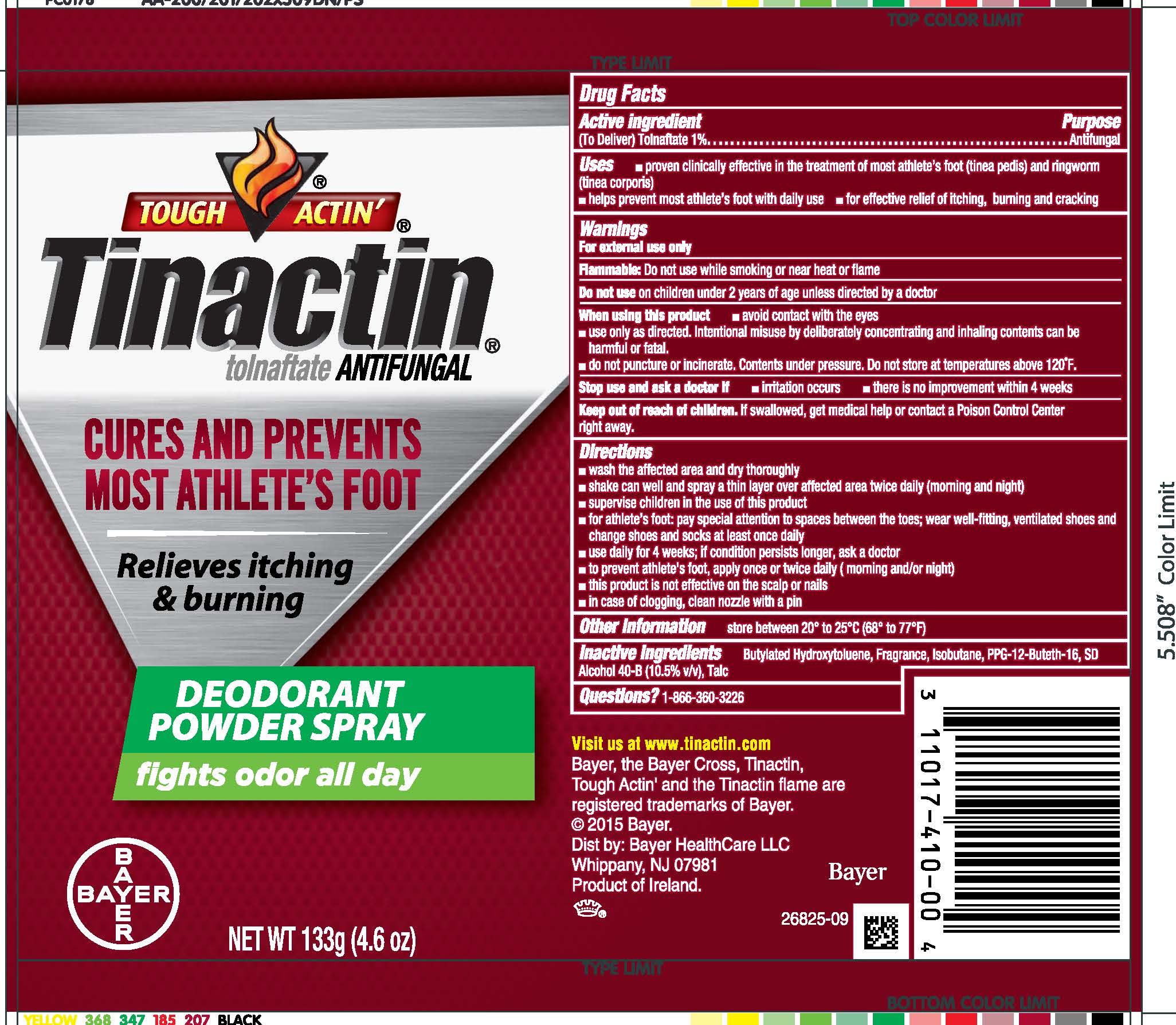 DRUG LABEL: Tinactin
NDC: 11523-4162 | Form: AEROSOL, POWDER
Manufacturer: Bayer HealthCare LLC.
Category: otc | Type: HUMAN OTC DRUG LABEL
Date: 20251205

ACTIVE INGREDIENTS: TOLNAFTATE 10 mg/1 g
INACTIVE INGREDIENTS: ISOBUTANE; PPG-12-BUTETH-16; TALC; BUTYLATED HYDROXYTOLUENE

Tinactin®
Antifungal

Drug Facts

Active ingredients

(To Deliver) Tolnaftate 1%

Purpose

Antifungal

Uses

- proven clinically effective in the treatment of most athlete's foot (tinea pedis) and ringworm (tinea corporis)
- helps prevent most athlete's foot with daily use
- for effective relief of itching, burning and cracking

Warnings

For external use only

DO NOT USE

Flammable:Do not use near heat, flame, or while smoking

Do not use on children under 2 years of age unless directed by a doctor

When using this product

- avoid contact with the eyes
- use only as directed. Intentional misuse by deliberately concentrating and inhaling the contents can be harmful or fatal.
- contents under pressure. do not puncture or incinerate. Do not store at temperatures above 120°F.

Stop use and ask a doctor if

- irritation occurs
- there is no improvement within 4 weeks

Keep out of reach of children. If swallowed, get medical help or contact a Poison Control Center right away.

Directions

- wash the affected area and dry thoroughly
- shake can well and spray a thin layer over affected area twice daily (morning and night)
- supervise children in the use of this product
- for athlete's foot: pay special attention to spaces between the toes; wear well-fitting, ventilated shoes and change shoes and socks at least once daily
- use daily for 4 weeks; if condition persists longer, ask a doctor
- to prevent athlete's foot, apply once or twice daily (morning and/or night)
- this product is not effective on the scalp or nails

Other information

- store between 20° to 25°C (68° to 77° F)

Inactive Ingredients

Butylated Hydroxytoluene, Fragrance, Isobutane, PPG-12-Buteth-16, SD Alcohol 40-B (10.5% v/v),Talc

Questions?

1-866-360-3266

PRINCIPAL DISPLAY PANEL - 133 g Can Label

NDC 11523-4162-1

TOUGH ACTIN'®
Tinactin ®

ANTIFUNGAL
tolnaftate

Cures and
prevents most
athlete's foot

DEODORANT
POWDER SPRAY
fights odor all day

Relieves itching & burning

NET WT 133g (4.6 oz)